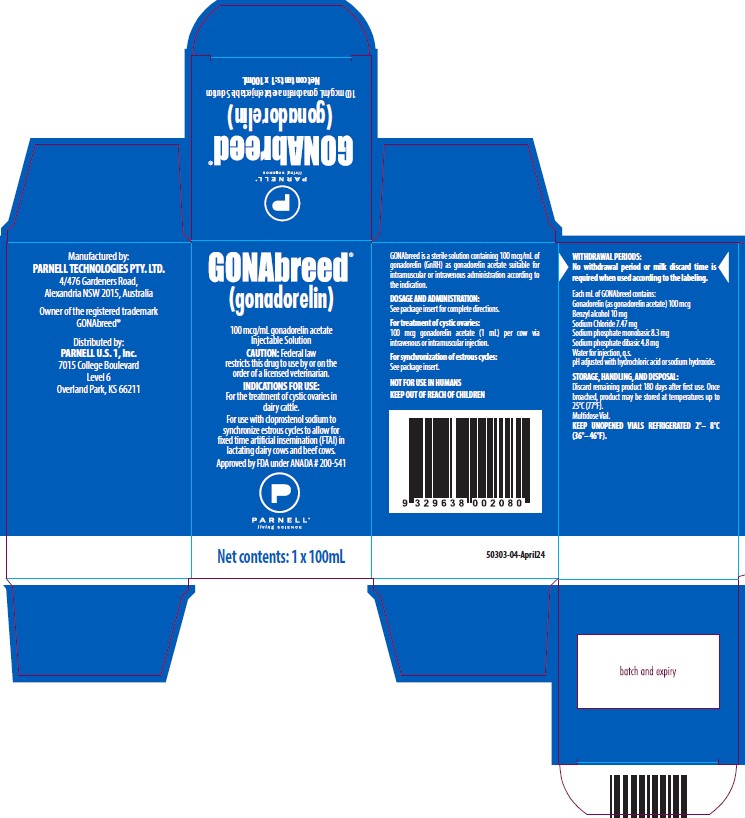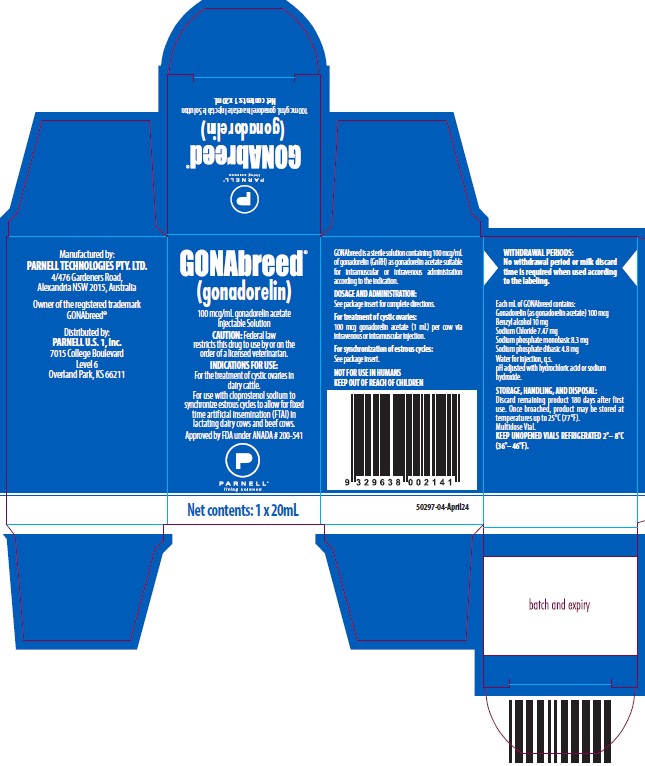 DRUG LABEL: GONABREED
NDC: 68504-002 | Form: INJECTION, SOLUTION
Manufacturer: Parnell Technologies Pty Ltd
Category: animal | Type: PRESCRIPTION ANIMAL DRUG LABEL
Date: 20251105

ACTIVE INGREDIENTS: GONADORELIN ACETATE 100 ug/1 mL
INACTIVE INGREDIENTS: BENZYL ALCOHOL 10 mg/1 mL; SODIUM CHLORIDE 7.47 mg/1 mL; SODIUM PHOSPHATE, MONOBASIC 8.3 mg/1 mL; SODIUM PHOSPHATE, DIBASIC 4.8 mg/1 mL; HYDROCHLORIC ACID; SODIUM HYDROXIDE; water

GONABREED

GONAbreed®

(gonadorelin)

100 mcg/mL gonadorelin acetate Injectable Solution

For the treatment of cystic ovaries in dairy cattle

For use with cloprostenol sodium to synchronize estrous cycles to allow for fixed time artificial insemination (FTAI) in lactating dairy cows and beef cows.

CAUTION: Federal (U.S.A.) law restricts this drug to use by or on the order of a licensed veterinarian.

DESCRIPTION:

GONAbreed is a sterile solution containing 100 micrograms of gonadorelin (GnRH) as gonadorelin acetate per milliliter suitable for intramuscular or intravenous administration according to the indication. Gonadorelin is a decapeptide composed of the sequence of amino acids –

5-oxoPro-His-Trp-Ser-Tyr-Gly-Leu-Arg-Pro-Gly-NH2 –

a molecular weight of 1182.32 and empirical formula C55H75N17O13. The acetate salt has a molecular weight of 60.05 and an empirical formula C55H75N17O13. C2H4O2.

Each mL of GONAbreed contains:
Gonadorelin (as gonadorelin acetate) 100 mcg
Benzyl alcohol 10 mg
Sodium chloride 7.47 mg
Sodium phosphate monobasic 8.3 mg
Sodium phosphate dibasic 4.8 mg
Water for injection, q.s.
pH adjusted with hydrochloric acid or sodium hydroxide.

Gonadorelin is the hypothalamic releasing factor responsible for the release of gonadotropins (e.g., luteinizing hormone [LH], follicle stimulating hormone [FSH]) from the anterior pituitary. Synthetic gonadorelin is physiologically and chemically identical to the endogenous bovine hypothalamic releasing factor.

INDICATIONS FOR USE:

Cystic Ovaries

GONAbreed is indicated for the treatment of ovarian follicular cysts in dairy cattle. Ovarian cysts are non-ovulated follicles with incomplete luteinization which result in nymphomania or irregular estrus.

Historically, cystic ovaries have responded to an exogenous source of LH such as human chorionic gonadotrophin. GONAbreed initiates release of endogenous LH to cause ovulation and luteinization.

Reproductive Synchrony

GONAbreed is indicated for use with cloprostenol sodium to synchronize estrous cycles to allow for fixed time artificial insemination (FTAI) in lactating dairy cows and beef cows.

DOSAGE AND ADMINISTRATION

Cystic Ovaries

The intravenous or intramuscular dosage of GONAbreed is 100 mcg gonadorelin acetate (1 mL) per cow.

Reproductive Synchrony

The intramuscular dosage of GONAbreed is 100 mcg gonadorelin acetate (1 mL) per cow, used in reproductive synchrony programs similar to the following:

1. Administer the first GONAbreed injection (1 mL) at Time 0.
2. Administer 500 mcg cloprostenol (as cloprostenol sodium) by intramuscular injection 6 to 8 days after the first GONAbreed injection.
3. Administer the second GONAbreed injection (1 mL) 30 to 72 hours after the cloprostenol sodium injection.
4. Perform FTAI 0 to 24 hours after the second GONAbreed injection, or inseminate cows on detected estrus using standard herd practices.

WARNINGS AND PRECAUTIONS:

Not for use in humans. Keep out of reach of children.

WITHDRAWAL PERIODS:
No withdrawal period or milk discard time is required when used according to the labeling.

To report suspected adverse drug events, for technical assistance or to obtain a copy of the Safety Data Sheet (SDS), contact Parnell at 1-800-88-PARNELL (1-800-887-2763). For additional information about adverse drug experience reporting for animal drugs, contact FDA at 1-888-FDA-VETS or http://www.fda.gov/reportanimalae.

PHARMACOLOGY AND TOXICOLOGY:

Endogenous gonadorelin is synthesized and/or released from the hypothalamus during various stages of the bovine estrous cycle following appropriate neurogenic stimuli. It passes via the hypophyseal portal vessels, to the anterior pituitary to effect the release of gonadotrophins (e.g. LH, FSH). Synthetic gonadorelin administered intravenously or intramuscularly also causes the release of endogenous LH or FSH from the anterior pituitary.

Gonadorelin acetate has been shown to be safe. The LD50 for mice and rats is greater than 60 mg/kg, and for dogs, greater than 600 mcg/kg, respectively. No adverse effects were noted among rats or dogs administered 120 mcg/kg/day or 72 mcg/kg/day intravenously for 15 days.

It has no adverse effects on heart rate, blood pressure, or EKG to unanesthetized dogs at 60 mcg/kg. In anesthetized dogs it did not produce depression of myocardial or system hemodynamics or adversely affect coronary oxygen supply or myocardial oxygen requirements.

The intravenous administration of 60 mcg/kg/day of gonadorelin acetate to pregnant rats and rabbits during organogenesis did not cause embryotoxic or teratogenic effects.

The intramuscular administration of 1,000 mcg to normally cycling dairy cattle had no effect on hematology or blood chemistry.

Further, gonadorelin did not cause irritation at the site of intramuscular administration in dogs with a dose of 72 mcg/kg/day for seven (7) days.

TARGET ANIMAL SAFETY:

In addition to the animal safety information presented in the PHARMACOLOGY and TOXICOLOGY section, the safety of gonadorelin was established through review and evaluation of extensive published literature available for the use of gonadorelin-containing products.

The intramuscular administration of 1000 mcg gonadorelin on five (5) consecutive days to normally cycling dairy cattle had no effect on hematology or clinical chemistries.

In field studies evaluating the effectiveness of gonadorelin for the treatment of ovarian follicular cysts, the incidence of health abnormalities was not significantly greater in cows administered gonadorelin than cows administered a placebo injection.

The target animal safety of, and injection site reactions to, GONAbreed when used with cloprostenol sodium were evaluated during the conduct of effectiveness field studies. The incidence of health abnormalities was not significantly greater in cows administered GONAbreed than cows administered a placebo injection.

EFFECTIVENESS:

The use of gonadorelin for treatment of ovarian follicular cysts in dairy cattle was demonstrated to be effective with a treatment dose of 100 mcg gonadorelin.

The effectiveness of GONAbreed (gonadorelin acetate) for use with cloprostenol sodium to synchronize estrous cycles to allow for FTAI in lactating dairy cows was demonstrated in a field study at 10 different locations in the U.S. Four of the locations represented conditions that would typically cause heat stress in lactating cows. A total of 1607 healthy, non-pregnant, primiparous or multiparous lactating dairy cows within 40-150 days postpartum were enrolled in the study. A total of 805 cows were administered GONAbreed (1 mL; 100 mcg gonadorelin as the acetate salt) and 802 cows were administered an equivalent volume of water for injection as an intramuscular injection twice in the following regimen:

Day 0: 1 mL GONAbreed or sterile water for injection
Day 7: 500 mcg cloprostenol (as cloprostenol sodium) Day 9: 1 mL GONAbreed or sterile water for injection

Fixed time AI was performed on Day 10, approximately 11 - 31 hours after the Day 9 injection. Cows were evaluated for pregnancy on Day 45 ± 5 days by trans-rectal ultrasound or rectal palpation. Pregnancy rate to FTAI was significantly higher (P < 0.0001) in cows treated with GONAbreed (33.4%) than the pregnancy rate to FTAI in cows treated with water (13.6%). The environmental condition (heat stress or not heat stress) did not affect the conclusion of effectiveness.

The effectiveness of GONAbreed (gonadorelin acetate) for use with cloprostenol sodium to synchronize estrous cycles to allow for FTAI in beef cows was demonstrated in a field study at 10 different locations in the U.S. A total of 706 healthy, non-pregnant, primiparous or multiparous beef cows within 40-150 days postpartum were enrolled in the study. A total of 364 cows were administered GONAbreed (1 mL; 100 mcg gonadorelin as the acetate salt) and 342 cows were administered an equivalent volume of water for injection as an intramuscular injection twice in the following regimen:

Day 0: 1 mL GONAbreed or sterile water for injection
Day 7: 500 mcg cloprostenol (as cloprostenol sodium) Day 9: 1 mL GONAbreed or sterile water for injection

Fixed time AI was performed immediately after the Day 9 injection. Cows were evaluated for pregnancy on Day 55 ± 5 days by trans-rectal ultrasound. Pregnancy rate to FTAI was significantly higher (P = 0.0006) in cows treated with GONAbreed (21.7%) than the pregnancy rate to FTAI in cows treated with water (7.4%).

HOW SUPPLIED:

GONAbreed is available in a concentration of 100 mcg/mL gonadorelin acetate.
GONAbreed is supplied in multidose vials containing 20 mL and 100 mL of sterile solution.

STORAGE, HANDLING, AND DISPOSAL:

Discard remaining product 180 days after first use. Once broached, product may be stored at temperatures up to 25°C (77°F). KEEP UNOPENED VIALS REFRIGERATED: 2° - 8°C (36° - 46°F).

Manufactured by:
PARNELL TECHNOLOGIES PTY. LTD.4/476 Gardeners Road Alexandria NSW 2015 Australia Owner of the registered trademark GONAbreed®

Distributed by:
PARNELL U.S. 1, Inc 7015 College Boulevard, Level 6 Overland Park, KS 66211

Approved by FDA under ANADA # 200-541

20mL & 100mL:
50428-01-April24

PRINCIPAL DISPLAY PANEL - 20 mL Carton

GONAbreed

(gonadorelin)

100 mcg/mL gonadorelin acetate
Injectable Solution

CAUTION: Federal (U.S.A.) law restricts this drug to use by or on the
order of a licensed veterinarian.

INDICATIONS FOR USE:
For the treatment of cystic ovaries in
dairy cattle.
For use with cloprostenol sodium to
synchronize estrous cycles to allow for fixed
time artificial insemination (FTAI) in
lactating dairy cows and beef cows.

APPROVED BY FDA UNDER ANADA # 200-541

PARNELL

living SCIENCE

Net contents: 1 x 20mL

PRINCIPAL DISPLAY PANEL - 100 mL Carton

GONAbreed

(gonadorelin)

100 mcg/mL gonadorelin acetate
Injectable Solution

CAUTION: Federal (U.S.A.) law restricts this drug to use by or on the
order of a licensed veterinarian.

INDICATIONS FOR USE:
For the treatment of cystic ovaries in
dairy cattle.
For use with cloprostenol sodium to
synchronize estrous cycles to allow for
fixed time artificial insemination (FTAI) in
lactating dairy cows and beef cows.

APPROVED BY FDA UNDER ANADA # 200-541

PARNELL

living SCIENCE

Net contents: 1 x 100mL